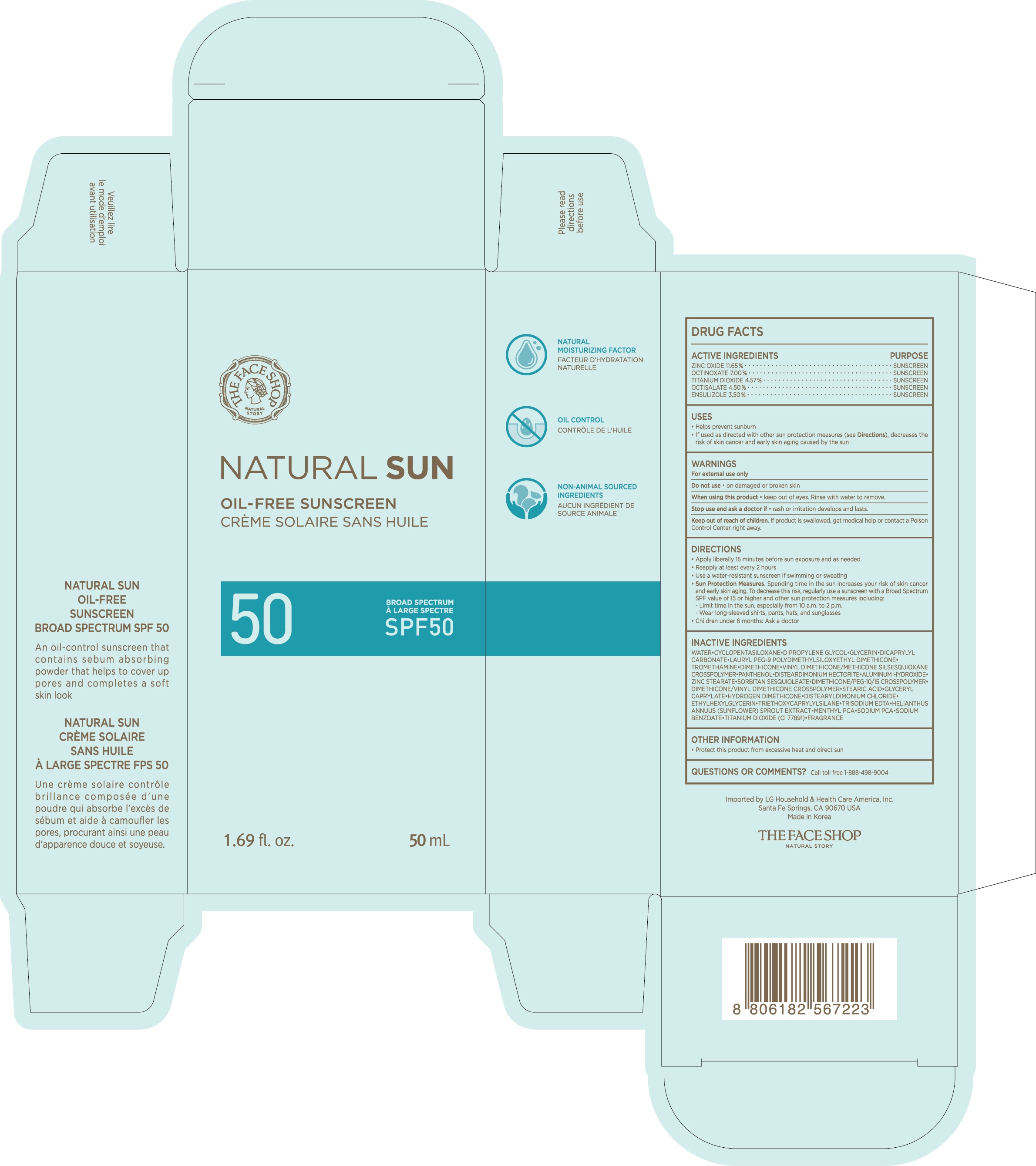 DRUG LABEL: THEFACESHOP Natural Sun Oil-Free Sunscreen Broad Spectrum SPF 50
NDC: 72330-195 | Form: LOTION
Manufacturer: fmg Co.Ltd
Category: otc | Type: HUMAN OTC DRUG LABEL
Date: 20250101

ACTIVE INGREDIENTS: OCTINOXATE 3.5 g/50 mL; ZINC OXIDE 5.825 g/50 mL; OCTISALATE 2.25 g/50 mL; TITANIUM DIOXIDE 2.285 g/50 mL; ENSULIZOLE 1.75 g/50 mL
INACTIVE INGREDIENTS: ETHYLHEXYLGLYCERIN; HELIANTHUS ANNUUS SPROUT; SODIUM PYRROLIDONE CARBOXYLATE; GLYCERIN; PANTHENOL; GLYCERYL CAPRYLATE; HYDROGEN DIMETHICONE (13 CST); EDETATE TRISODIUM; DICAPRYLYL CARBONATE; LAURYL PEG-9 POLYDIMETHYLSILOXYETHYL DIMETHICONE; DIMETHICONE; VINYL DIMETHICONE/METHICONE SILSESQUIOXANE CROSSPOLYMER; MENTHYL DL-PYRROLIDONECARBOXYLATE; TRIETHOXYCAPRYLYLSILANE; SODIUM BENZOATE; WATER; DIMETHICONE CROSSPOLYMER (450000 MPA.S AT 12% IN CYCLOPENTASILOXANE); DIMETHICONE/VINYL DIMETHICONE CROSSPOLYMER (HARD PARTICLE); ZINC STEARATE; SORBITAN SESQUIOLEATE; ALUMINUM HYDROXIDE; DISTEARYLDIMONIUM CHLORIDE; DIPROPYLENE GLYCOL; TROMETHAMINE; STEARIC ACID

72330-195-01 THEFACESHOP Natural Sun Oil-Free Sunscreen Broad Spectrum SPF 50

ACTIVE INGREDIENTS

Ensulizole 3.5%
Octinoxate 7.00%
Octisalate 4.5%
Titanium Dioxide 4.57%
Zinc Oxide 11.65%

PURPOSE

SUNSCREEN

USES

- Helps prevent sunburn
- If used as directed with other sun protection measures (see Directions), decreases the risk of skin cancer and early skin aging caused by the sun

WARNINGS

For external use only

Do not useon damaged or broken skin

WHEN USING

When using this productkeep out of eyes. Rinse with water to remove

Stop use and ask doctorif rash occurs

Keep out of reach of children.If product is swallowed, get medical help or contact a Poison Control Center right away.

DIRECTIONS

- Apply liberally 15 minutes before sun exposure and as needed.
- Reapply as needed or after towel drying, swimming, or sweating.
- Sun Protection Measures.Spending time in the sun increases your risk of skin cancer and early skin aging. To decrease this risk, regularly use a sunscreen with a Broad Spectrum SPF value of 15 or higher and other sun protection measures including:

- Limit time in the sun, especially from 10 a.m. to 2 p.m.

- Wear long-sleeved shirts, pants, hats, and sunglasses

- Children under 6 months: Ask a doctor

INACTIVE INGREDIENTS

WATER, CYCLOPENTASILOXANE, DIPROPYLENE GLYCOL, GLYCERIN, DICAPRYLYL CARBONATE, LAURYL PEG-9 POLYDIMETHYLSILOXYETHYL DIMETHICONE, TROMETHAMINE, DIMETHICONE, VINYL DIMETHICONE/METHICONE SILSESQUIOXANE CROSSPOLYMER, PANTHENOL, DISTEARDIMONIUM HECTORITE, ALUMINUM HYDROXIDE, ZINC STEARATE, SORBITAN SESQUIOLEATE, DIMETHICONE/PEG-10/15 CROSSPOLYMER, DIMETHICONE/VINYL DIMETHICONE CROSSPOLYMER, STEARIC ACID, GLYCERYL CAPRYLATE, HYDROGEN DIMETHICONE, DISTEARYLDIMONIUM CHLORIDE, ETHYLHEXYLGLYCERIN, TRIETHOXYCAPRYLYLSILANE, TRISODIUM EDTA, HELIANTHUS ANNUS (SUNFLOWER) SRPOUT EXTRACT, MENTHYL PCA, SODIUM PCA, SODIUM BENZOATE, TITANIUM DIOXIDE (CI 77891), FRAGRANCE

OTHER INFORMATION

Protect this product from excessive heat and direct sun

QUESTIONS OR COMMENTS?

Call toll free 1-888-498-9004